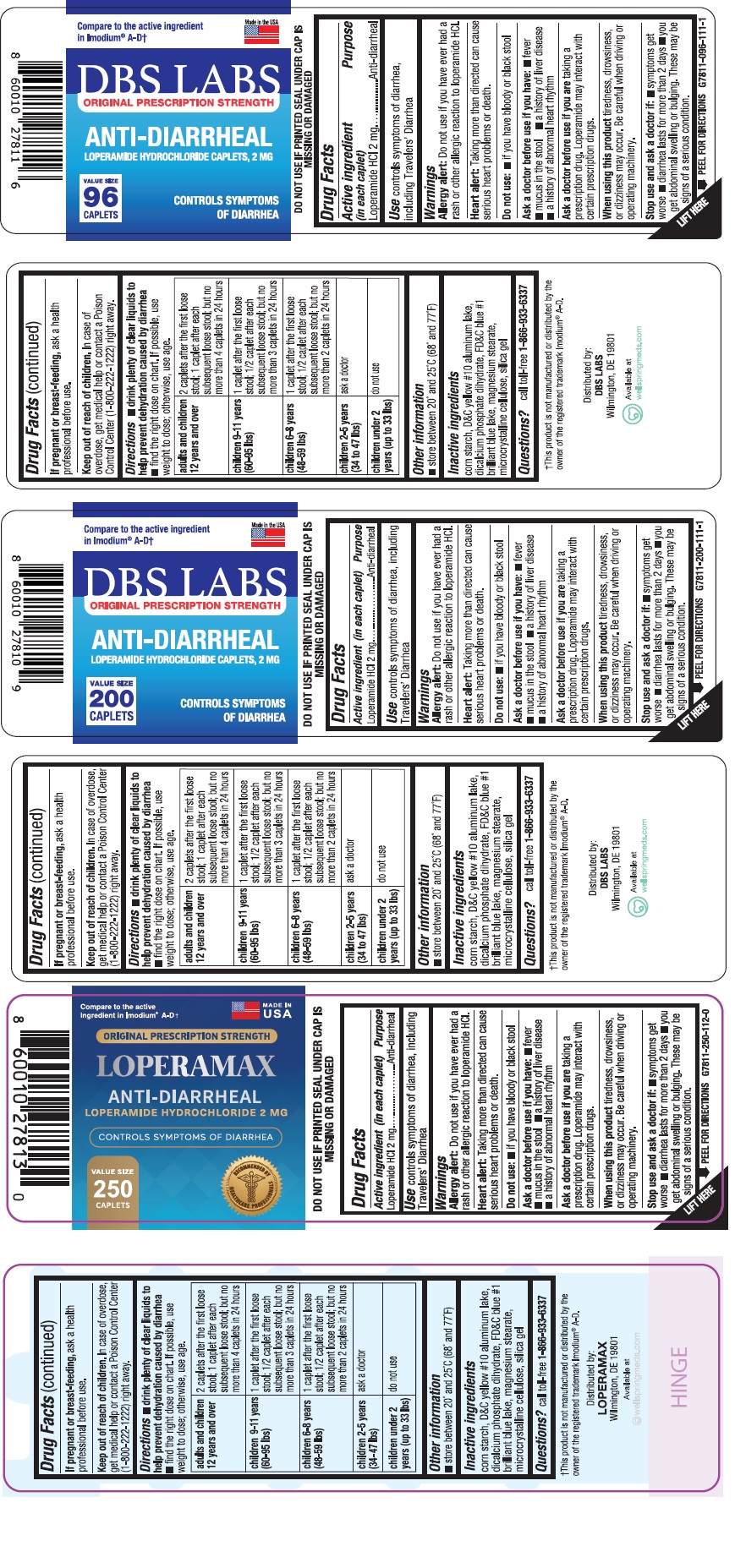 DRUG LABEL: Anti-Diarrheal
NDC: 84441-711 | Form: TABLET
Manufacturer: IMO-GEN LABS LLC
Category: otc | Type: HUMAN OTC DRUG LABEL
Date: 20260204

ACTIVE INGREDIENTS: LOPERAMIDE HYDROCHLORIDE 2 mg/1 1
INACTIVE INGREDIENTS: STARCH, CORN; D&C YELLOW NO. 10 ALUMINUM LAKE; DIBASIC CALCIUM PHOSPHATE DIHYDRATE; FD&C BLUE NO. 1 ALUMINUM LAKE; MAGNESIUM STEARATE; MICROCRYSTALLINE CELLULOSE; SILICON DIOXIDE

ANTI-DIARRHEAL
Loperamide Hydrochloride Caplets, 2 mg

Active ingredient (in each caplet)

Loperamide HCl 2 mg

Purpose

Anti-diarrheal

Use

Controls symptoms of diarrhea, including Travelers' Diarrhea

Warnings

Allergy alert: Do not use if you have ever had a rash or other allergic reaction to loperamide HCl.

Heart alert: Taking more than directed can cause serious heart problems or death.

Do not use:

- if you have bloody or black stool.

Ask a doctor before use if you have:

- fever
- mucus in the stool
- a history of liver disease
- a history of abnormal heart rhythm

Ask a doctor before use if you are

taking a prescription drug. Loperamide may interact with certain prescription drugs.

When using this product

tiredness, drowsiness, or dizziness may occur. Be careful when driving or operating machinery.

Stop use and ask a doctor if

- symptoms get worse
- diarrhea lasts more than 2 days
- you get abdominal swelling or bulging. These may be signs of a serious condition.

If pregnant or breast-feeding,

ask a health professional before use.

Keep out of reach of children.

In case of overdose, get medical help or contact a Poison Control Center (1-800-222-1222) right away.

Directions

- drink plenty of clear liquid to help prevent dehydration caused by diarrhea
- find right dose on chart. If possible, use weight to dose; otherwise, use age.

adults and children 12 years and over | 2 caplets after the first loose stool; 1 caplet after each subsequent loose stool; but no more than 4 caplets in 24 hours
children 9-11 years (60-95 lbs) | 1 caplet after the first loose stool; 1/2 caplet after each subsequent loose stool; but no more than 3 caplets in 24 hours
children 6-8 years (48-59 lbs) | 1 caplet after the first loose stool; 1/2 caplet after each subsequent loose stool; but no more than 2 caplets in 24 hours
children 2-5 years (34-47 lbs) | ask a doctor
children under 2 years (up to 33 lbs) | do not use

Other information

- store between 20° and 25°C (68° and 77°F)

Inactive ingredients

corn starch, D&C yellow #10 aluminum lake, dibasic calcium phosphate dihydrate, FD&C blue#1 brilliant blue, magnesium stearate, microcrystalline cellulose, silica gel

Questions?

call toll-free 1-866-933-6337

Distributed by:

IBS LABS

Wilmington, DE 19801

Principal Display Panel

Compare to the active ingredient in Imodium®A-D†

Anti-Diarrheal

Loperamide Hydrocholoride Caplets, 2 mg

Controls Symptoms of Diarrhea

†This product is not manufactured or distributed by the owner of the registered trademark Imodium®A-D.